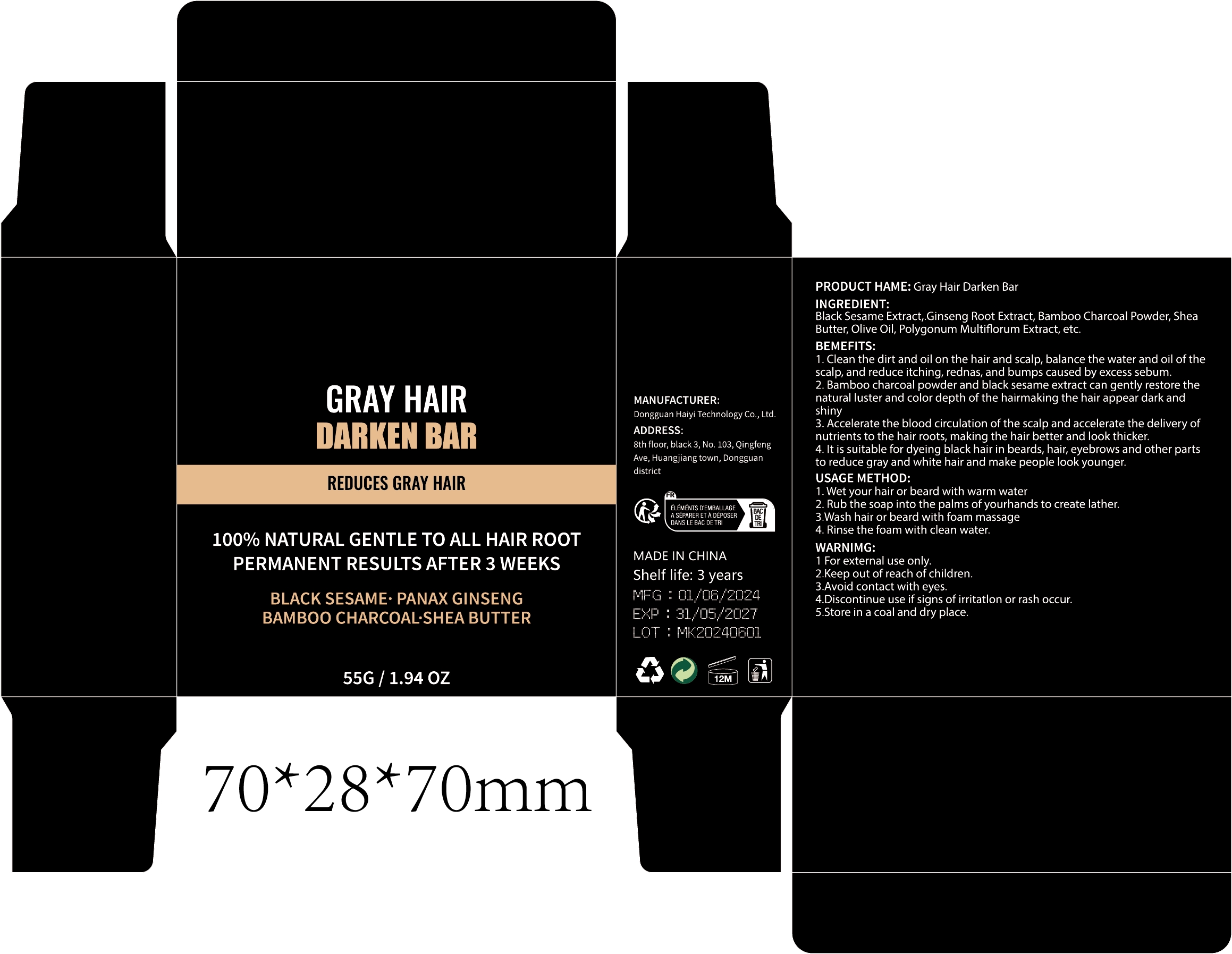 DRUG LABEL: Gray Hair Darken Bar
NDC: 84732-030 | Form: SOAP
Manufacturer: Dongguan Haiyi Technology Co.,Ltd.
Category: otc | Type: HUMAN OTC DRUG LABEL
Date: 20241007

ACTIVE INGREDIENTS: SESAMUM INDICUM WHOLE 1 mg/100 g
INACTIVE INGREDIENTS: OLIVE OIL; ACTIVATED CHARCOAL; SHEA BUTTER; REYNOUTRIA MULTIFLORA ROOT OIL; PANAX GINSENG ROOT OIL

Active ingredient

Black Sesame Extract

Inactive ingredient

Ginseng Root Extract, Bamboo Charcoal Powder, Shea Butter, Olive Oil, Polygonum Multiflorum Extract, etc.

Purpose section

1. Clean the dirt and oil on the hair and scalp, balance the water and oil of the scalp, and reduce itching, rednas, and bumps caused by excess sebum.
2. Bamboo charcoal powder and black sesame extract can gently restore the natural luster and color depth of the hairmaking the hair appear dark and shiny
3. Accelerate the blood circulation of the scalp and accelerate the delivery of nutrients to the hair roots, making the hair better and look thicker.
4. lt is suitable for dyeing black hair in beards, hair, eyebrows and other parts to reduce gray and white hair and make people look younger.

Warning

1 For external use only.
2.Keep out of reach of children.
3.Avoid contact with eyes.
4.Discontinue use if signs of irritatlon or rash occur.
5.Store in a coal and dry place.

stop use

This product may cause allergic reactions in as mall number of people.
lf you experience any discomfort,please stop using it immediately.

not use

Not suitable for use by children, pregnantor breast feeding people.

OUT OF CHILDREN

KEEP THE PRODUCT OUT OF REACH OF CHILDREN to

HOW TO USE

1.Wet your hair or beard with warm water
2. Rub the soap into the palms of yourhands to create lather,
3.Wash hair or beard with foam massage
4.Rinse the foam with clean water.

Dosage

take an appropriateamount,Use 2-3 times a week